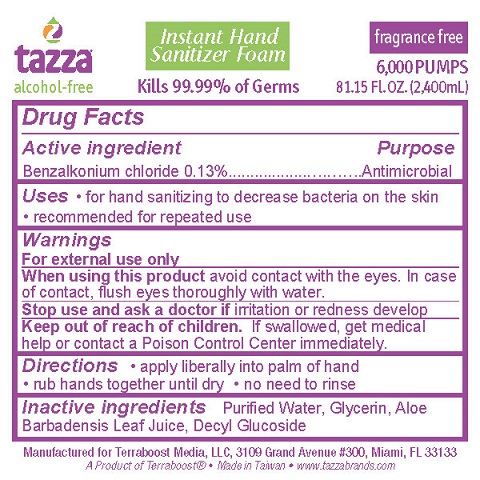 DRUG LABEL: Hand Sanitizer
NDC: 76370-0002 | Form: LIQUID
Manufacturer: Tazza Brands East Inc.
Category: otc | Type: HUMAN OTC DRUG LABEL
Date: 20220517

ACTIVE INGREDIENTS: BENZALKONIUM CHLORIDE 0.13 g/100 mL
INACTIVE INGREDIENTS: WATER; GLYCERIN; ALOE VERA LEAF; DECYL GLUCOSIDE

TAZZA INSTANT HAND SANITIZER FOAM

Drug Facts

Active ingredient

Benzalkonium Chloride 0.13%

Purpose

Antimicrobial

Uses

- for hand sanitizing to decrease bacteria on skin
- recommended for repeated use

Warnings

For external use only

When using this product avoid contact with the eyes. In case of eye contact, flush eyes with water.

Stop use and ask a doctor if irritation or redness develop

Keep out of reach of children. If swallowed, get medical help or contact a Poison Control Center immediately.

Directions

- apply liberally into palm of hand
- rub hands together until dry
- no need to rinse

INACTIVE INGREDIENT

Inactive ingredients Purified Water, Glycerin, Aloe Barbadensis Leaf Juice, Decyl Glucoside

Manufactured for Terraboost Media, LLC, 3109 Grand Avenue #300, Miami, FL 33133

www.tazzabrands.com

A Product of Terraboost® • or Made in Taiwan • www.tazzabrands.com

PACKAGE LABEL

Tazza Instant Hand Sanitizer Foam

fragrance free

alcohol-free

Kills 99.99% of Germs

6000 PUMPS

81.15 Fl. OZ. (2,400mL)